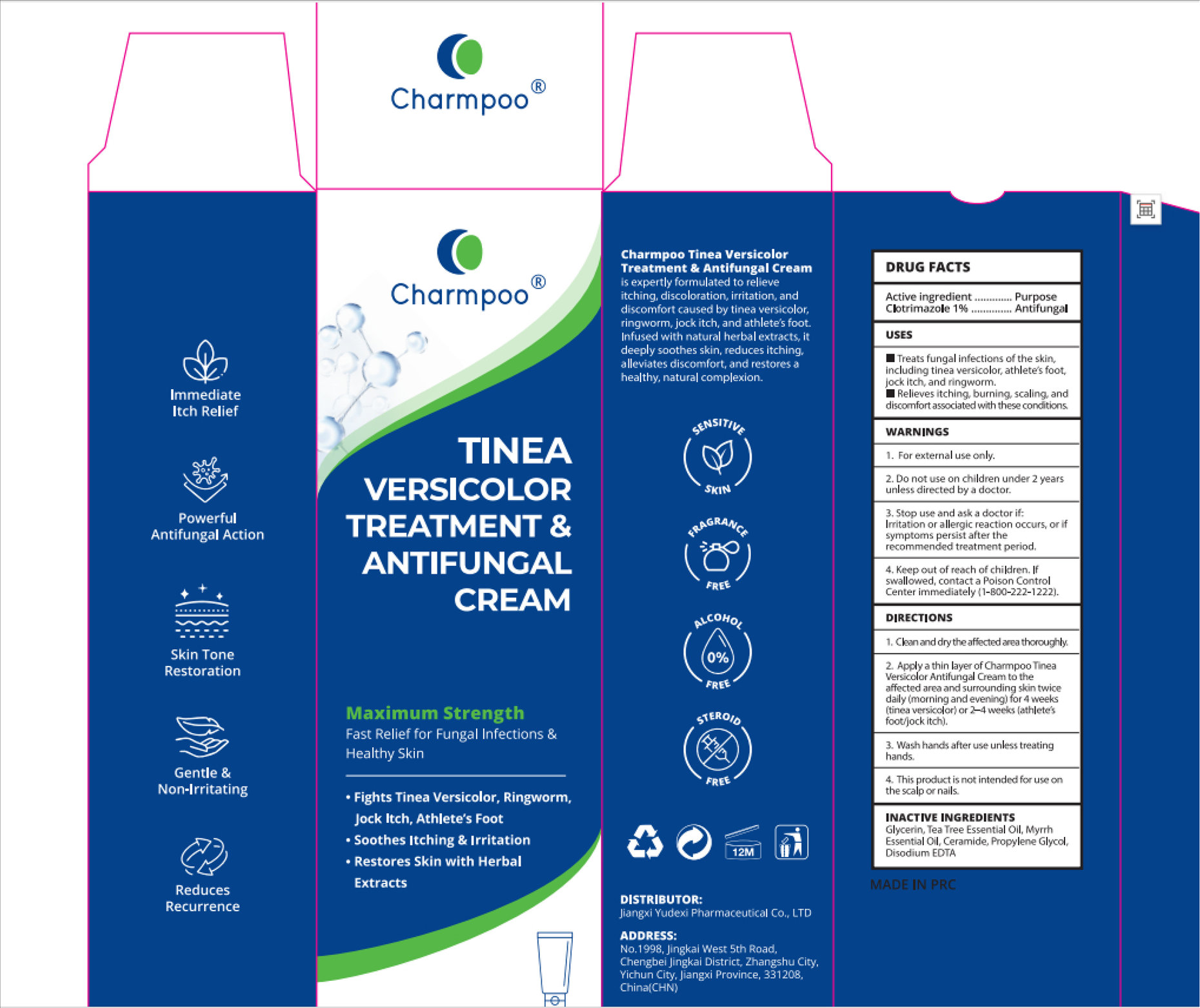 DRUG LABEL: Charmpoo TINEA VERSICOLOR TREATMENT ANTIFUNGAL
NDC: 85248-143 | Form: CREAM
Manufacturer: Jiangxi Yudexi Pharmaceutical Co., LTD
Category: otc | Type: HUMAN OTC DRUG LABEL
Date: 20260214

ACTIVE INGREDIENTS: CLOTRIMAZOLE 1 g/100 g
INACTIVE INGREDIENTS: EDETATE DISODIUM; MYRRH OIL; PROPYLENE GLYCOL; GLYCERIN; CERAMIDE AP; TEA TREE OIL

85248-143

Active Ingredient

Clotrimazole 1%

Purpose

Antifungal

Use

Treats fungal infections of the skin,including tinea versicolor, athlete's foot,jock itch, and ringworm. Relieves itching, burning, scaling, anddiscomfort associated with these conditions

Warnings

For external use only

Do not use on children under 2 yearsunless directed by a doctor.

When Using

. Stop use and ask a doctor if:Irritation or allergic reaction occurs, or ifsymptoms persist after therecommended treatment period.

Stop Use

. Stop use and ask a doctor if:Irritation or allergic reaction occurs, or ifsymptoms persist after therecommended treatment period.

Ask Doctor

. Stop use and ask a doctor if:Irritation or allergic reaction occurs, or ifsymptoms persist after therecommended treatment period.

Keep Oot Of Reach Of Children

Ifswallowed, contact a Poison ControlCenter immediately(1-800-222-1222)

Directions

1. Clean and dry the affected area thoroughly 2. Apply a thin layer of Charmpoo Tinea Versicolor Antifungal Cream to theaffected area and surrounding skin twicedaily (morning and evening)for 4 weeks(tinea versicolor)or 2-4 weeks (athlete'sfoot/jock itch) 3. Wash hands after use unless treatinghands. 4. This product is not intended for use on the scalp or nails.

Inactive ingredients

Glycerin, Tea Tree Essential Oil, MyrrhEssential Oil, Ceramide, Propylene Glycol,Disodium EDTA